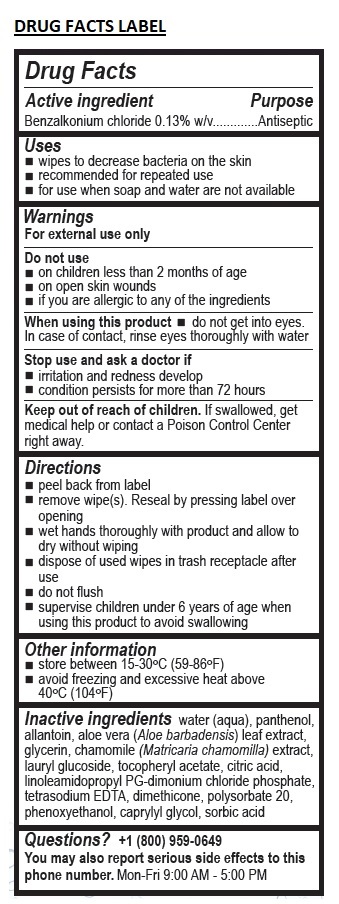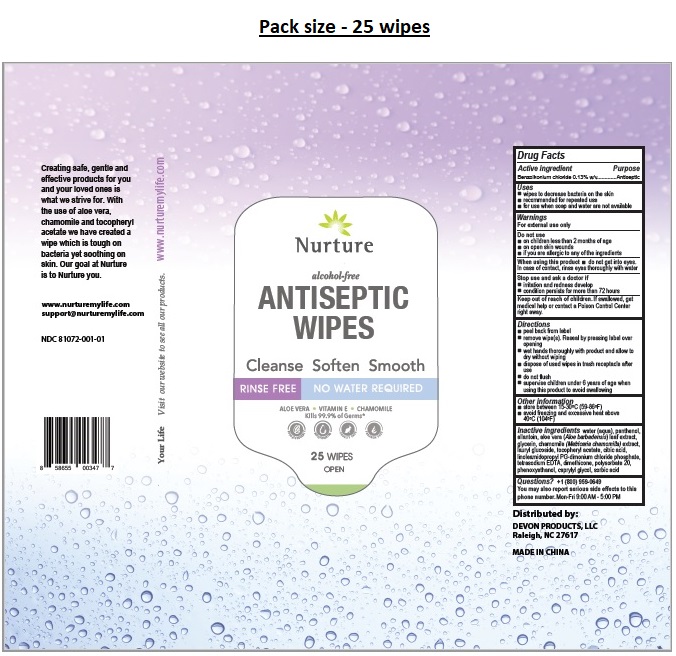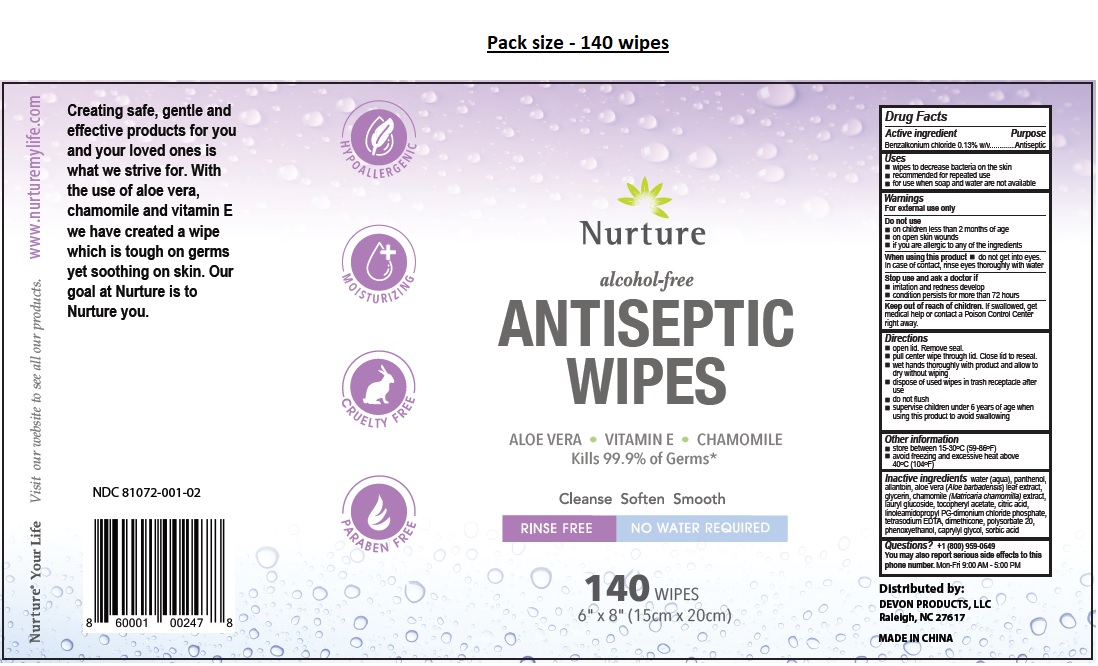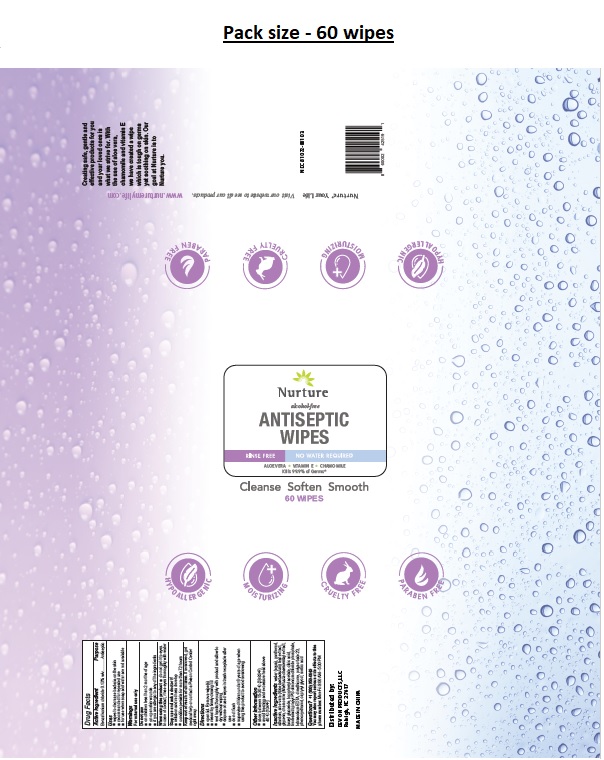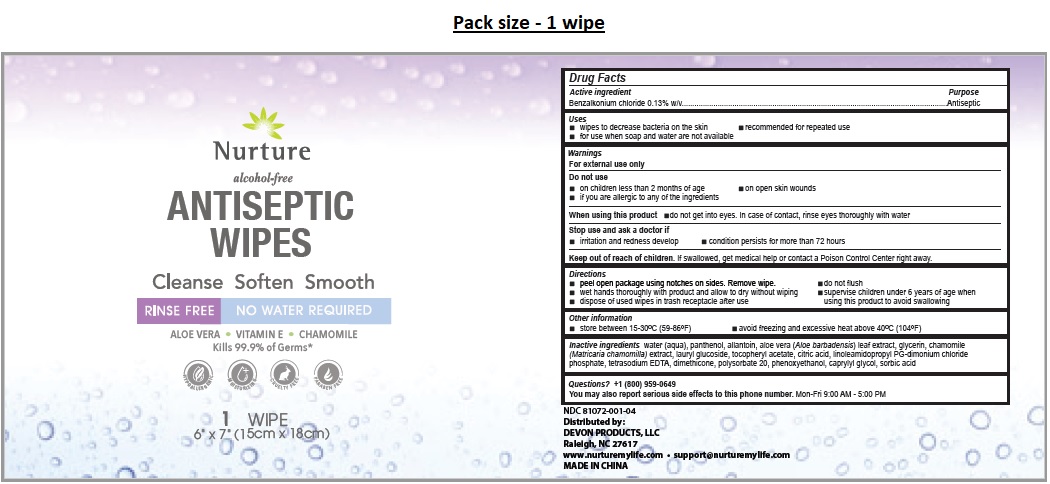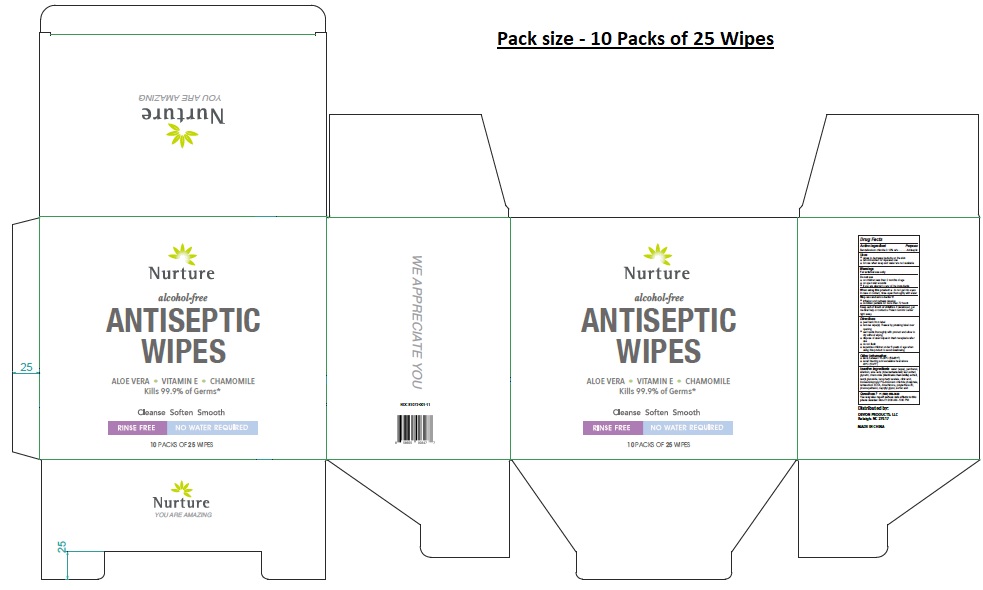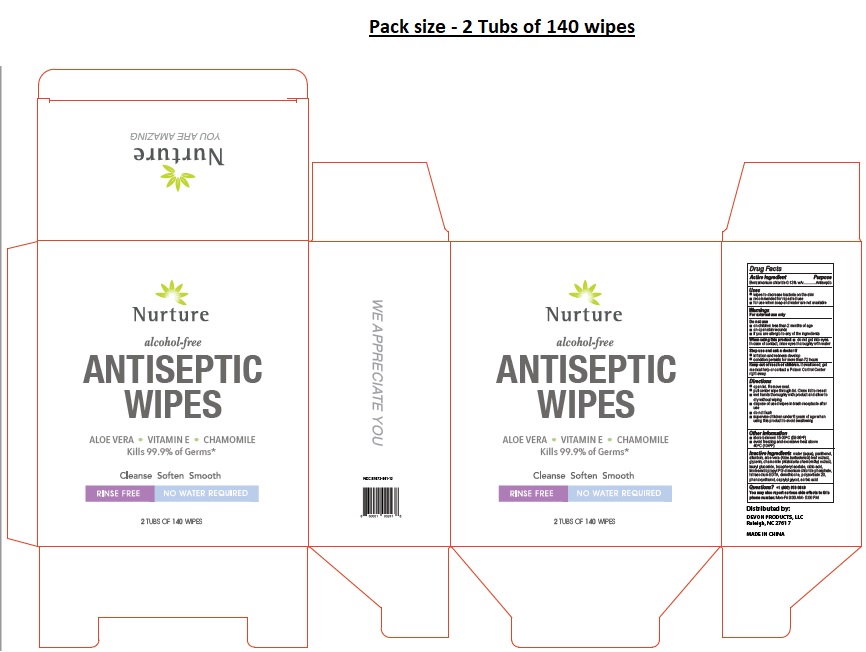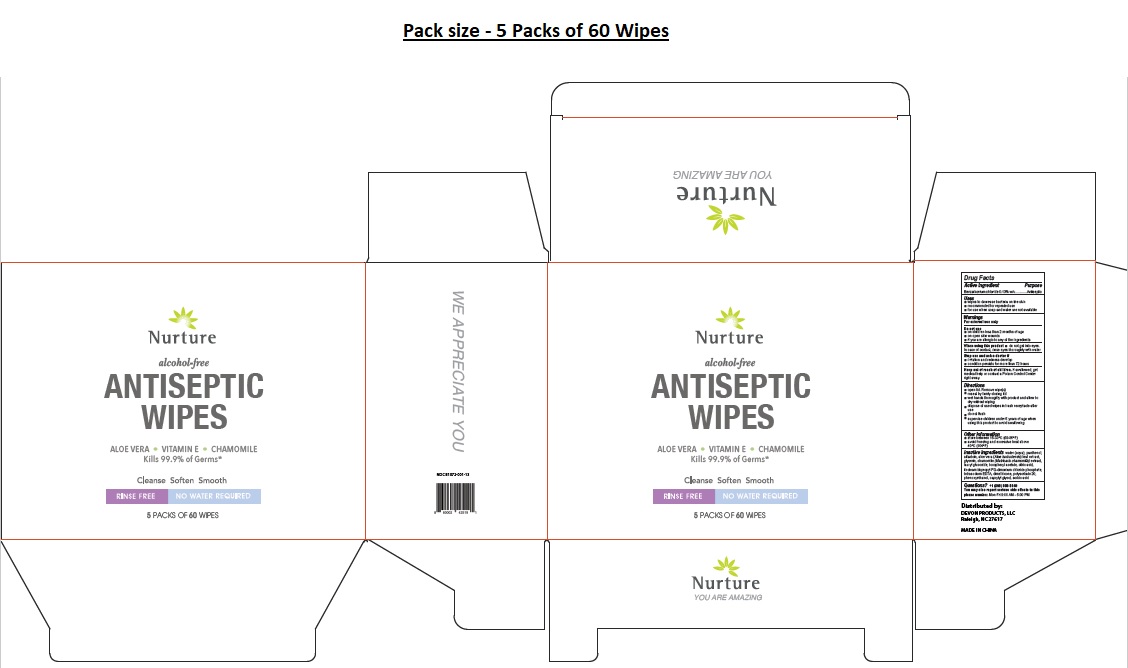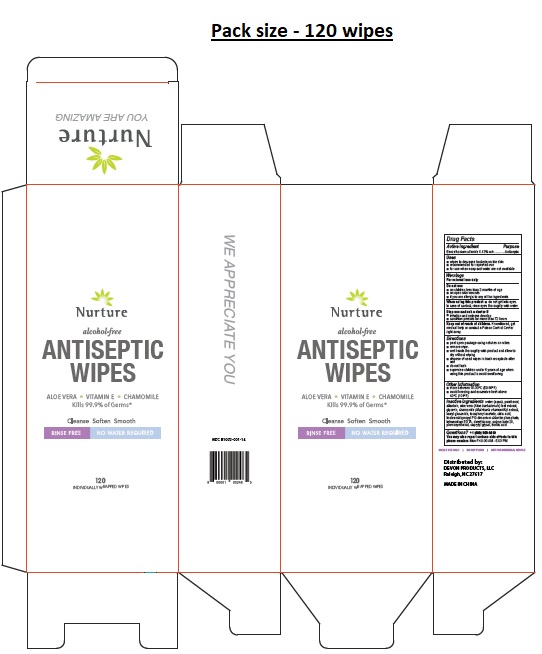 DRUG LABEL: Nurture ANTISEPTIC WIPES
NDC: 81072-001 | Form: CLOTH
Manufacturer: Devon Products, LLC
Category: otc | Type: HUMAN OTC DRUG LABEL
Date: 20250402

ACTIVE INGREDIENTS: BENZALKONIUM CHLORIDE 0.13 g/100 mL
INACTIVE INGREDIENTS: WATER; PANTHENOL; ALLANTOIN; ALOE VERA LEAF; GLYCERIN; CHAMOMILE; LAURYL GLUCOSIDE; .ALPHA.-TOCOPHEROL ACETATE; CITRIC ACID MONOHYDRATE; LINOLEAMIDOPROPYL PROPYLENE GLYCOL-DIMONIUM CHLORIDE PHOSPHATE; EDETATE SODIUM; DIMETHICONE, UNSPECIFIED; POLYSORBATE 20; PHENOXYETHANOL; CAPRYLYL GLYCOL; SORBIC ACID

Nurture ANTISEPTIC WIPES

Active ingredient

Benzalkonium chloride 0.13% w/v

Purpose

Antiseptic

Uses

• wipes to decrease bacteria on the skin
• recommended for repeated use
• for use when soap and water are not available

Warnings

For external use only

Do not use

• on children less than 2 months of age
• on open skin wounds
• if you are allergic to any of the ingredients

When using this product • do not get into eyes. In case of contact, rinse eyes thoroughly with water

Stop use and ask a doctor if
• irritation and redness develop
• condition persists for more than 72 hours

Keep out of reach of children. If swallowed, get medical help or contact a Poison Control Center right away.

Directions

• peel back from label
• remove wipe(s). Reseal by pressing label over opening
• wet hands thoroughly with product and allow to dry without wiping
• dispose of used wipes in trash receptacle after use
• do not flush
• supervise children under 6 years of age when using this product to avoid swallowing

Other information

• store between 15-30ºC (59-86ºF)
• avoid freezing and excessive heat above 40ºC (104ºF)

Inactive ingredients

water (aqua), panthenol, allantoin, aloe vera (Aloe barbadensis) leaf extract, glycerin, chamomile (Matricaria chamomilla) extract, lauryl glucoside, tocopheryl acetate, citric acid, linoleamidopropyl PG-dimonium chloride phosphate, tetrasodium EDTA, dimethicone, polysorbate 20, phenoxyethanol, caprylyl glycol, sorbic acid

Questions? +1 (800) 959-0649

You may also report serious side effects to this phone number. Mon-Fri 9:00 AM - 5:00 PM

alcohol-free

ALOE VERA • VITAMIN E • CHAMOMILE
Kills 99.9% of Germs*

Cleanse Soften Smooth

RINSE FREE NO WATER REQUIRED

YOU ARE AMAZING

WE APPRECIATE YOU

SINGLE USE ONLY | DO NOT FLUSH | NOT FOR INDIVIDUAL RESALE

Creating safe, gentle and effective products for you and your loved ones is what we strive for. With the use of aloe vera, chamomile and vitamin E we have created a wipe which is tough on germs yet soothing on skin. Our goal at Nurture is to Nurture you.

HYPOALLERGENIC

MOISTURIZING

CRUELTY FREE

PARABEN FREE

Nuture* Your Life Visit our website to see all our products. www.nurturemylife.com

support@nurturemylife.com

Distributed by:
DEVON PRODUCTS, LLC
Raleigh, NC 27617

MADE IN CHINA